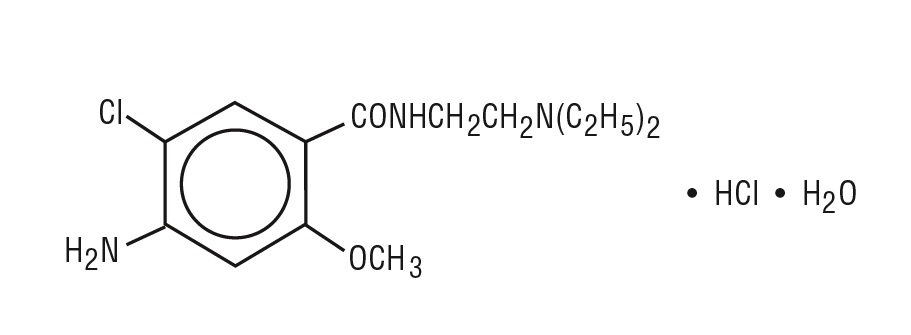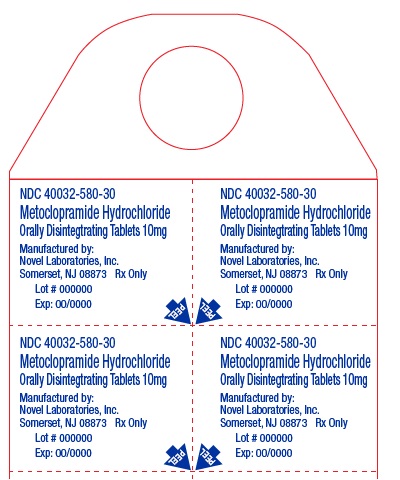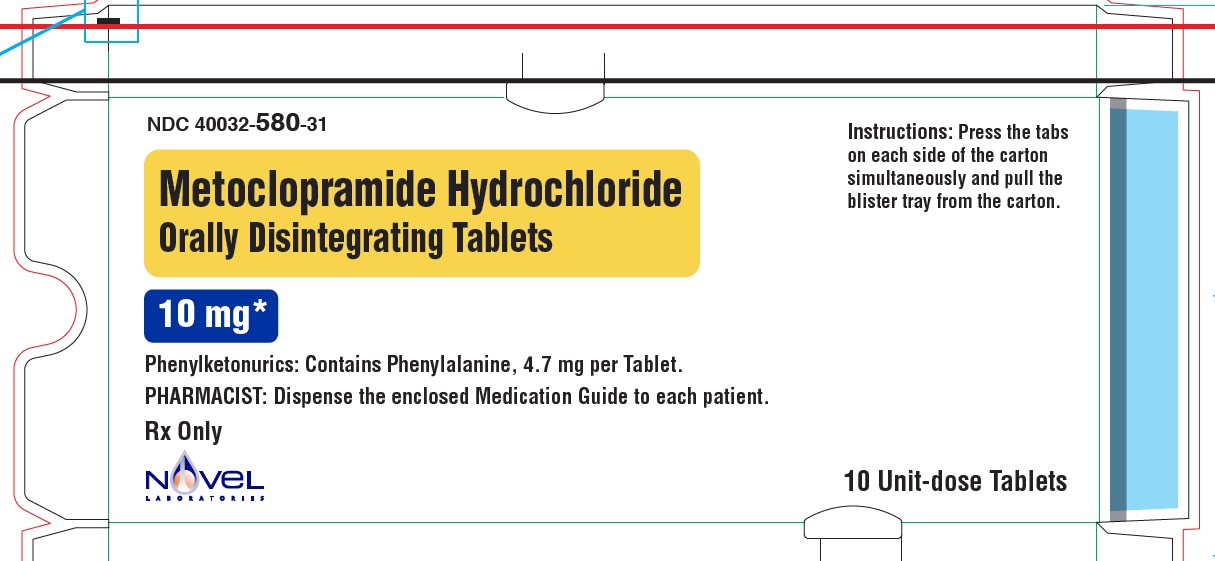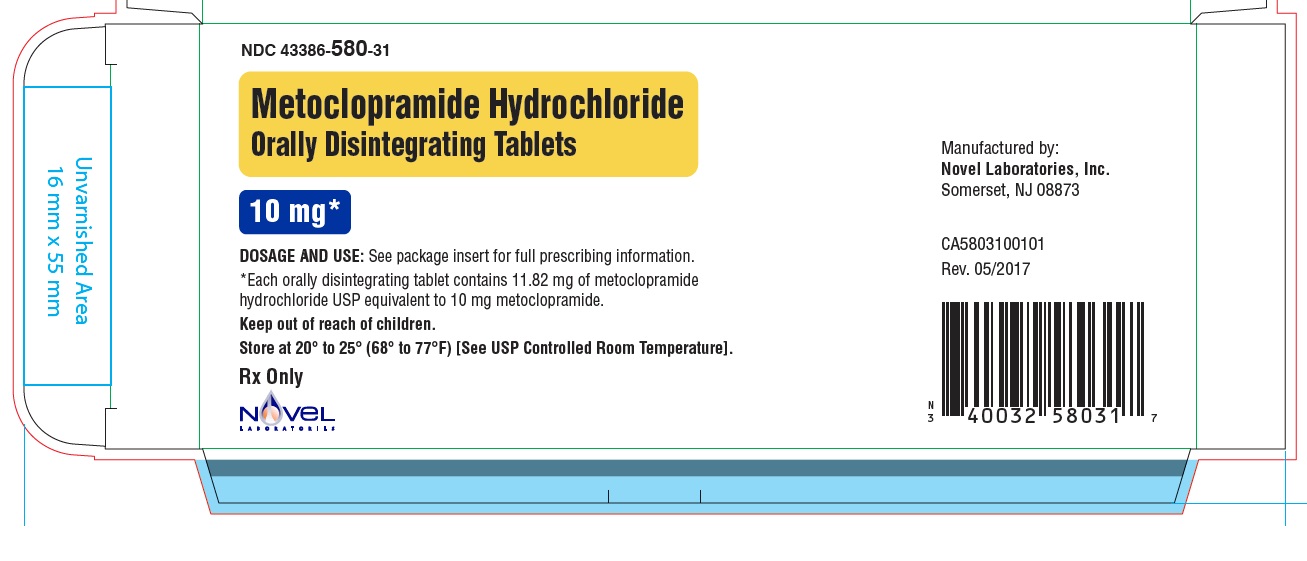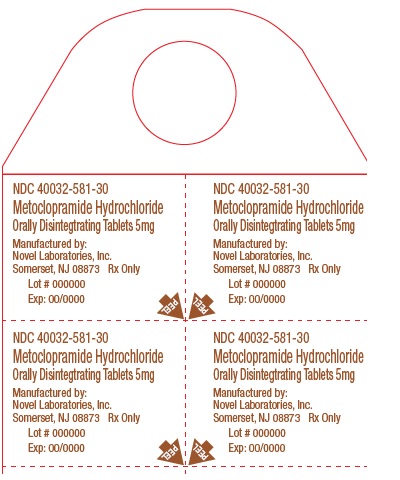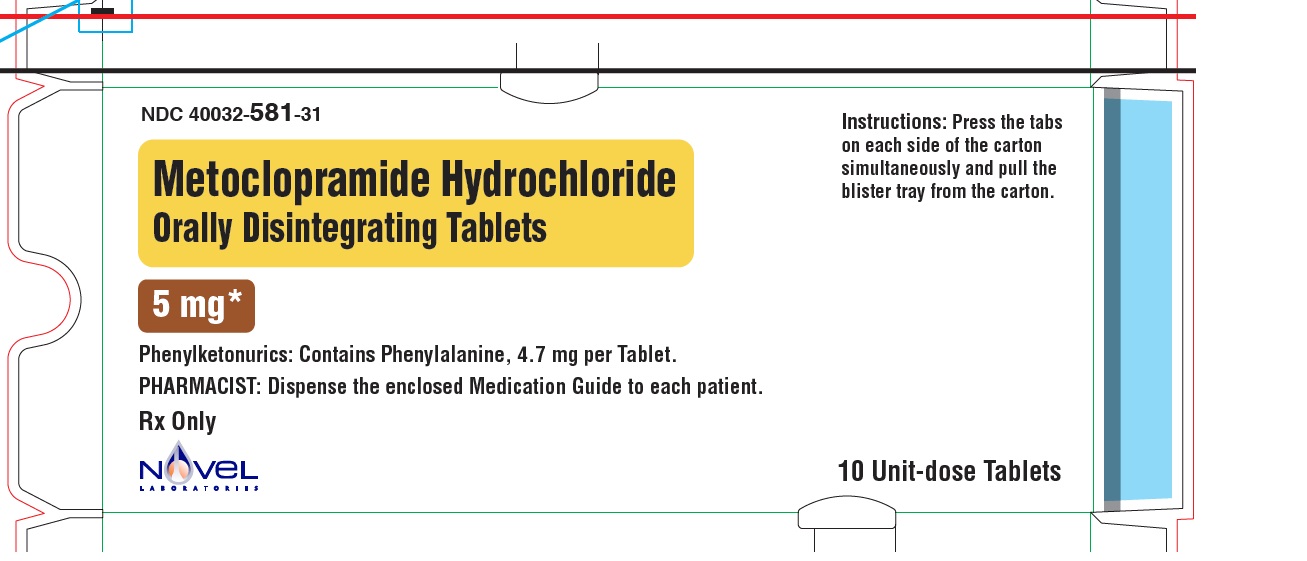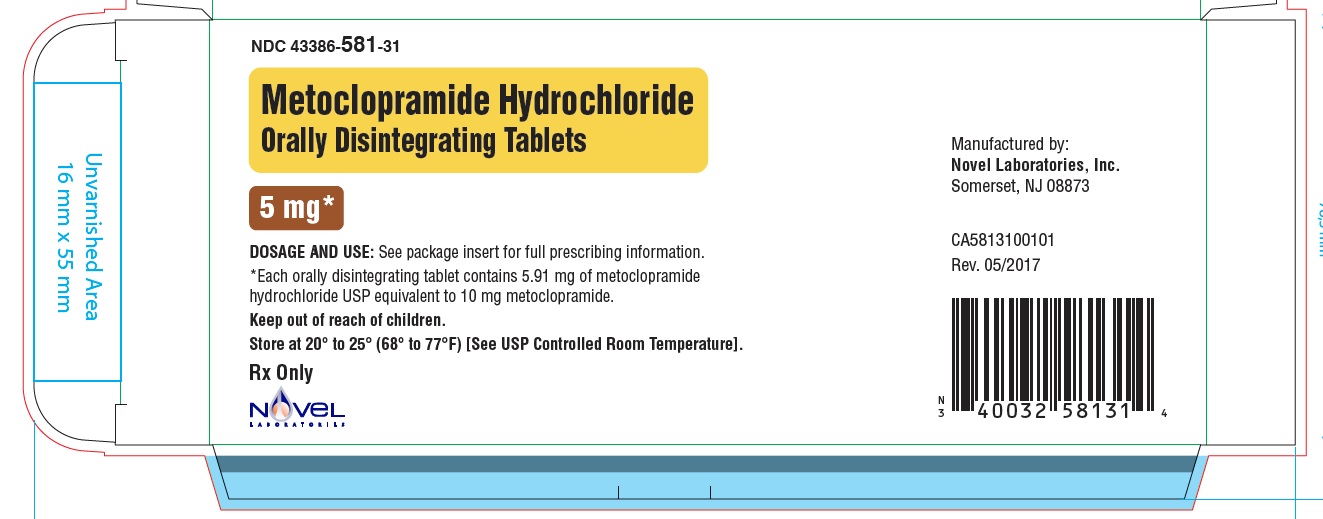 DRUG LABEL: METOCLOPRAMIDE hydrochloride
NDC: 40032-580 | Form: TABLET, ORALLY DISINTEGRATING
Manufacturer: Novel Laboratories, Inc.
Category: prescription | Type: HUMAN PRESCRIPTION DRUG LABEL
Date: 20170523

ACTIVE INGREDIENTS: METOCLOPRAMIDE HYDROCHLORIDE 10 mg/1 1
INACTIVE INGREDIENTS: PHOSPHORIC ACID; MANNITOL; CELLULOSE, MICROCRYSTALLINE; SILICON DIOXIDE; BUTYLATED HYDROXYANISOLE; BUTYLATED HYDROXYTOLUENE; CROSPOVIDONE; ASPARTAME; MAGNESIUM STEARATE; STARCH, CORN; DIMETHYLAMINOETHYL METHACRYLATE - BUTYL METHACRYLATE - METHYL METHACRYLATE COPOLYMER

HIGHLIGHTS OF PRESCRIBING INFORMATION

These highlights do not include all the information needed to use METOCLOPRAMIDE hydrochloride safely and effectively. See full prescribing information for METOCLOPRAMIDE hydrochloride.
METOCLOPRAMIDE hydrochloride (Metoclopramide Hydrochloride) TABLET, ORALLY DISINTEGRATING for ORAL use.
Initial U.S. Approval: 1976

WARNING: TARDIVE DYSKINESIA

See full prescribing information for complete boxed warning.

Treatment with metoclopramide can cause tardive dyskinesia, a serious movement disorder that is often irreversible. The risk of developing tardive dyskinesia increases with the duration of treatment and the total cumulative dose.

Metoclopramide therapy should be discontinued in patients who develop signs or symptoms of tardive dyskinesia. There is no known treatment for tardive dyskinesia. In some patients, symptoms may lessen or resolve after metoclopramide treatment is stopped.

Treatment with metoclopramide for longer than 12 weeks should be avoided in all but rare cases where therapeutic benefit is thought to outweigh the risk of developing tardive dyskinesia. (5.1)

1 INDICATIONS AND USAGE

Metoclopramide Orally Disintegrating Tablets are a dopamine receptor antagonist indicated for:

- Relief of Symptomatic Gastroesophageal Reflux: short-term (4 to 12 weeks) therapy for adults with symptomatic, documented gastroesophageal reflux who fail to respond to conventional therapy (1.1)
- Diabetic Gastroparesis (Diabetic Gastric Stasis): the relief of symptoms in adults associated with acute and recurrent diabetic gastroparesis (gastric stasis) (1.2)

Important Limitations:

- Therapy should not exceed 12 weeks in duration (1.3)
- Metoclopramide Hydrochloride Orally Disintegrating Tablets are recommended only for adults. The safety and effectiveness in pediatric patients have not been established (1.3)

2 DOSAGE AND ADMINISTRATION

- Gastroesophageal Refulx Disease: 10 mg to 15 mg dose up to four times daily at least 30 minutes before eating and at bedtime (2.2)
- Diabetic Gastroparesis (Diabetic Gastric Stasis): 10 mg dose four times daily at least 30 minutes before eating and at bedtime for two to eight weeks (2.3)

3 DOSAGE FORMS & STRENGTHS

Orally Disintegrating Tablets: 5 mg and 10 mg (3)

4 CONTRAINDICATIONS

- Intestinal Obstruction, Hemorrhage, or Perforation (4.1)
- Pheochromocytoma (4.2)
- Known Sensitivity or Intolerance (4.3)
- Epilepsy (4.4)
- Concomitant Medications with Extrapyramidal Reactions (4.5)

5 WARNINGS AND PRECAUTIONS

- Tardive Dyskinesia (5.1)
- Acute Dystonic Reactions, Drug-induced Parkinsonism and Other Extrapyramidal Symptoms (5.2)
- Neuroleptic Malignant Syndrome (5.3)
- Depression (5.4)
- Hypertension (5.5)
- Congestive Heart Failure and Ventricular Arrhythmia (5.6)
- Withdrawal from Metoclopramide (5.7)

6 ADVERSE REACTIONS

The most common adverse reactions (>2%) are headache, nausea, vomiting, fatigue, and somnolence (6.1).

To report SUSPECTED ADVERSE REACTIONS, contact Novel Laboratories, Inc. at 1-866-403-7592 or FDA at 1-800-FDA-1088 or www.fda.gov/medwatch.

7 DRUG INTERACTIONS

- Anticholinergic drugs : Antagonize effects of metoclopramide (7.1)
- Narcotic analgesic drugs : May increase sedation (7.1)
- Monoamine oxidase inhibitors : May cause hypertensive crisis (due to catecholamine release) (7.2)
- Altered drug absorption : May decrease absorption of drugs from the stomach and increase absorption of drugs from the small bowel (7.3)
- Insulin : Changes in food transit time may require adjustment of insulin dose or timing to avoid hypoglycemia (7.4)
- Antidepressants, Antipsychotics, and Neuroleptics : Concomitant use with metoclopramide is associated with increased risk of tardive dyskinesia and Neuroleptic Malignant Syndrome (7.5)

8 USE IN SPECIFIC POPULATIONS

- Pediatric Use : The safety and effectiveness of Metoclopramide Hydrochloride Orally Disintegrating Tablets in pediatric patients have not been established (8.4)
- Geriatric Use : Elderly patients may be more sensitive to adverse reactions such as sedation and drug-induced movement disorders. (8.5)
- Impaired Renal Function : Initial dosing may need to be reduced and titrated (8.6).

FULL PRESCRIBING INFORMATION

WARNING: TARDIVE DYSKINESIA

Treatment with metoclopramide can cause tardive dyskinesia, a serious movement disorder that is often irreversible. The risk of developing tardive dyskinesia increases with the duration of treatment and the total cumulative dose.

Metoclopramide therapy should be discontinued in patients who develop signs or symptoms of tardive dyskinesia. There is no known treatment for tardive dyskinesia. In some patients, symptoms may lessen or resolve after metoclopramide treatment is stopped.

Treatment with metoclopramide for longer than 12 weeks should be avoided in all but rare cases where therapeutic benefit is thought to outweigh the risk of developing tardive dyskinesia.

[See Warnings and Precautions (5.1)]

1 INDICATIONS AND USAGE

1.1 Symptomatic Gastroesophageal Reflux Disease

Metoclopramide Hydrochloride Orally Disintegrating Tablets are indicated as short-term (4 to 12 weeks) therapy for adults with symptomatic, documented gastroesophageal reflux disease (GERD) who fail to respond to conventional therapy.

1.2 Diabetic Gastroparesis (Diabetic Gastric Stasis)

Metoclopramide Hydrochloride Orally Disintegrating Tablets are indicated for the relief of symptoms associated with acute and recurrent diabetic gastroparesis (gastric stasis) in adults.

1.3 Important Limitations

Metoclopramide Hydrochloride Orally Disintegrating Tablets are indicated for adults only. Therapy should not exceed 12 weeks in duration. The safety and effectiveness in pediatric patients have not been established.

2 DOSAGE AND ADMINISTRATION

2.1 Important Instructions for Use

Take on an empty stomach at least 30 minutes before eating since food can decrease the peak concentrations of drug in the bloodstream and/or the time it takes to achieve the maximum drug level in the bloodstream [see Clinical Pharmacology (12.3)]. Do not repeat dose if inadvertently taken with food.

Since the tablet absorbs moisture rapidly, only remove each dose from the packaging just prior to taking. Handle the tablet with dry hands and place on the tongue. If the tablet should break or crumble while handling, discard and remove a new tablet.

Metoclopramide Hydrochloride Orally Disintegrating Tablet disintegrates on the tongue in approximately one minute (with a range of 10 seconds to 14 minutes). Metoclopramide Hydrochloride Orally Disintegrating Tablet is designed to be taken without liquid; however, the effect on the pharmacokinetics of Metoclopramide Hydrochloride Orally Disintegrating Tablets taken with liquid is unknown.

2.2 Symptomatic Gastroesophageal Reflux Disease

For the relief of symptomatic, documented gastroesophageal reflux disease (GERD), therapy should not exceed 12 weeks in duration.

Take 10 mg to 15 mg dose of Metoclopramide Hydrochloride Orally Disintegrating Tablets up to four times daily (e.g., at least 30 minutes before each meal and at bedtime). Doses may vary depending upon the symptoms being treated and the clinical response. If symptoms only occur intermittently or at specific times of the day, metoclopramide may be used in single doses up to 20 mg prior to the symptoms rather than continuous treatment.

Since there is a poor correlation between symptomatic relief and healing of esophageal lesions, any therapy directed at esophageal lesions is best confirmed by endoscopic evaluation. Although experience with the effects of metoclopramide on esophageal erosions and ulcerations is limited, healing was documented in a controlled trial using four times daily therapy at 15 mg/dose. Prolonged treatment (>12 weeks) with metoclopramide should be avoided in all but rare cases where therapeutic benefit is thought to counterbalance the risks to the patient of developing tardive dyskinesia. [see Warnings and Precautions (5.1)]

2.3 Diabetic Gastroparesis (Diabetic Gastric Stasis)

For the relief of symptoms associated with diabetic gastroparesis (diabetic gastric stasis), therapy of two to eight weeks is recommended. Therapy should not exceed 12 weeks in duration.

Take a 10 mg dose of Metoclopramide Hydrochloride Orally Disintegrating Tablets up to four times a day (e.g., at least 30 minutes before each meal and at bedtime).

The initial route of administration should be determined by the severity of the presenting symptoms. If only the earliest manifestations of diabetic gastric stasis are present, oral administration of Metoclopramide Hydrochloride Orally Disintegrating Tablets may be initiated. However, if severe symptoms are present, therapy should begin with metoclopramide injection.

Administration of metoclopramide injection up to 10 days may be required before symptoms subside, at which time oral administration may be instituted. Since diabetic gastric stasis is frequently recurrent, Metoclopramide Hydrochloride Orally Disintegrating Tablets therapy should be reinstituted at the earliest manifestation.

2.4 Renal Impairment

Some patients, such as the elderly or those with impaired kidney function (creatinine clearance below 40 mL/min) may be more sensitive to the therapeutic dose or the adverse effects of metoclopramide. Therefore, these patients should start therapy at a lower dose (approximately half the recommended dosage) and the dose should be titrated according to their overall clinical response and/or adverse event profile. Dialysis is not likely to be an effective method of drug removal in overdose situations.

3 DOSAGE FORMS & STRENGTHS

5 mg Tablets: Metoclopramide Hydrochloride Orally Disintegrating Tablets are round, white to off-white, flat faced beveled edge tablet, debossed with 'N' on one side and "581" on the other side.

10 mg Tablets: Metoclopramide Hydrochloride Orally Disintegrating Tablets are round, white to off-white, flat faced beveled edge tablet, debossed with 'N' on one side and "580" on the other side.

4 CONTRAINDICATIONS

4.1 Intestinal Obstruction, Hemorrhage, or Perforation

Do not use metoclopramide whenever stimulation of gastrointestinal motility may be dangerous such as in the presence of gastrointestinal hemorrhage, mechanical obstruction, or perforation.

4.2 Pheochromocytoma

Metoclopramide is contraindicated in patients with pheochromocytoma because the drug may precipitate a hypertensive crisis, most likely due to release of catecholamines from the tumor. Such hypertensive crises may be controlled by phentolamine.

4.3 Known Sensitivity or Intolerance

Metoclopramide is contraindicated in patients with known sensitivity or intolerance to the drug.

4.4 Epilepsy

Do not use metoclopramide in patients with epilepsy since the frequency and severity of seizures may be increased.

4.5 Concomitant Medications with Extrapyramidal Reactions

Do not use metoclopramide in patients receiving other drugs which are likely to cause extrapyramidal reactions, since the frequency and severity of extrapyramidal reactions may be increased [see Warnings and Precautions (5.2), Adverse Reactions (6.2) and Drug Interactions (7.5)].

5 WARNINGS AND PRECAUTIONS

5.1 Tardive Dyskinesia

[see Boxed Warning]

Treatment with metoclopramide can cause tardive dyskinesia (TD), a potentially irreversible and disfiguring disorder characterized by involuntary movements of the face, tongue, or extremities. The risk of developing tardive dyskinesia increases with the duration of treatment and the total cumulative dose. An analysis of utilization patterns showed that about 20% of patients who used metoclopramide took it for longer than 12 weeks. Treatment with metoclopramide for longer than the recommended 12 weeks should be avoided in all but rare cases where therapeutic benefit is thought to outweigh the risk of developing TD.

Although the risk of developing TD in the general population may be increased among the elderly, women, and diabetics, it is not possible to predict which patients will develop metoclopramide-induced TD. Both the risk of developing TD and the likelihood that TD will become irreversible increase with duration of treatment and total cumulative dose.

Metoclopramide should be discontinued in patients who develop signs or symptoms of TD. There is no known effective treatment for established cases of TD, although in some patients, TD may remit, partially or completely, within several weeks to months after metoclopramide is withdrawn.

Metoclopramide itself may suppress, or partially suppress, the signs of TD, thereby masking the underlying disease process. The effect of this symptomatic suppression upon the long-term course of TD is unknown. Therefore, metoclopramide should not be used for the symptomatic control of TD.

5.2 Acute Dystonic Reactions, Drug-induced Parkinsonism, and Other Extrapyramidal Symptoms

Extrapyramidal symptoms (EPS), manifested primarily as acute dystonic reactions, occur in approximately 1 in 500 patients treated with the usual adult dosages of 30 to 40 mg/day of metoclopramide. These usually are seen during the first 24 to 48 hours of treatment with metoclopramide, occur more frequently in pediatric patients and adult patients less than 30 years of age and are even more frequent at higher doses. These symptoms may include involuntary movements of limbs and facial grimacing, torticollis, oculogyric crisis, rhythmic protrusion of tongue, bulbar type of speech, trismus, or dystonic reactions resembling tetanus. Rarely, dystonic reactions may present as stridor and dyspnea, possibly due to laryngospasm. If these symptoms occur, inject 50 mg diphenhydramine hydrochloride intramuscularly. Benztropine mesylate, 1 to 2 mg intramuscularly, may also be used to reverse these reactions.

Drug-induced Parkinsonism can occur during metoclopramide therapy, more commonly within the first 6 months after beginning treatment, but also after longer periods. Parkinsonian symptoms generally subside within 2 to 3 months following discontinuation of metoclopramide. Patients with a history of Parkinson's disease should be given metoclopramide cautiously, if at all, since such patients can experience exacerbation of Parkinsonian symptoms when taking metoclopramide.

5.3 Neuroleptic Malignant Syndrome

There have been rare reports of an uncommon but potentially fatal symptom complex sometimes referred to as Neuroleptic Malignant Syndrome (NMS) associated with metoclopramide. Clinical manifestations of NMS include hyperthermia, muscle rigidity, altered consciousness, and evidence of autonomic instability (irregular pulse or blood pressure, tachycardia, diaphoresis and cardiac arrhythmias). The diagnostic evaluation of patients with this syndrome is complicated. In arriving at a diagnosis, it is important to identify cases where the clinical presentation includes both serious medical illness (e.g., pneumonia, systemic infection) and untreated or inadequately treated extrapyramidal signs and symptoms (EPS). Other important considerations in the differential diagnosis include central anticholinergic toxicity, heat stroke, malignant hyperthermia, drug fever and primary central nervous system (CNS) pathology. The management of NMS should include immediate discontinuation of metoclopramide and other drugs not essential to concurrent therapy; intensive symptomatic treatment and medical monitoring; and, treatment of any concomitant serious medical problems for which specific treatments are available. Bromocriptine and dantrolene sodium have been used in treatment of NMS, but their effectiveness has not been established [see Adverse Reactions (6)].

5.4 Depression

Depression associated with metoclopramide use has occurred in patients with and without a history of depression. Symptoms ranged from mild to severe and included suicidal ideation and suicide. For those patients with a prior history of depression, metoclopramide should only be given if the expected benefits outweigh the potential risks.

5.5 Hypertension

In one study in hypertensive patients, intravenously administered metoclopramide was shown to release catecholamines; hence, caution should be exercised when metoclopramide is used in patients with hypertension. There are also clinical reports of hypertensive crises in some patients with undiagnosed pheochromocytoma, thus any rapid rise in blood pressure associated with Metoclopramide Hydrochloride Orally Disintegrating Tablets use should result in immediate cessation of metoclopramide use in those patients [see Contraindications (4.2)].

5.6 Congestive Heart Failure and Ventricular Arrhythmia

Since metoclopramide produces a transient increase in plasma aldosterone, patients with cirrhosis or congestive heart failure may be at risk of developing fluid retention and volume overload. If these side effects occur at any time in any patients during metoclopramide therapy, the drug should be discontinued.

5.7 Withdrawal from Metoclopramide

Adverse reactions, especially those involving the nervous system, may occur after stopping the use of Metoclopramide Hydrochloride Orally Disintegrating Tablets. A small number of patients may experience withdrawal symptoms after stopping that could include dizziness, nervousness, and/or headaches.

Phenylketonurics:

Phenylalanine is a component of aspartame. Each 5 mg and 10 mg Metoclopramide Hydrochloride Orally Disintegrating Tablets contains 4.7 mg of phenylalanine.

6 ADVERSE REACTIONS

6.1 Clinical Trials Experience

Because clinical trials are conducted under widely varying conditions, adverse reaction rates observed in the clinical trials of a drug cannot be directly compared to rates in the clinical studies of another drug and may not reflect the rates observed in clinical practice.

A total of 86 subjects entered three studies with Metoclopramide Hydrochloride Orally Disintegrating Tablets; 12 subjects entered a pilot bioavailability study (BA); 44 subjects entered a bioequivalence (BE) study, and 30 subjects entered a food-effect study. The adverse reactions from the BE and food-effect study are summarized in Table 1. The pilot BA study data are not included because it was performed with a formulation different from the Metoclopramide Hydrochloride Orally Disintegrating Tablets formulation.

The adverse experience profile seen with Metoclopramide Hydrochloride Orally Disintegrating Tablets was similar to metoclopramide tablets. Thirty-three (33) adverse reactions were reported after receiving Metoclopramide Hydrochloride Orally Disintegrating Tablets and 30 adverse reactions were reported after receiving metoclopramide tablets.

Table 1: Adverse Reactions in BE and Food-Effect Study in ≥2% of Subjects

Adverse Reaction | Metoclopramide Hydrochloride Orally Disintegrating TabletsN^1,3 (%)^2 | Metoclopramide tabletsN^1,4 (%)^2
Nausea | 4 (4.2 %) | 4 (5.6 %)
Vomiting | 2 (2.1 %) | 1 (1.4 %)
Fatigue | 2 (2.1 %) | 2 (2.8 %)
Headache | 5 (5.2 %) | 3 (4.2 %)
Somnolence | 2 (2.1 %) | 2 (2.8 %)
Dizziness | 1 (1.0 %) | 3 (4.2 %)

^1 N = number of subjects that reported adverse reactions

^2 Percent (%) occurrence = N divided by number of subjects dosed with respective study drug

^3 Number of subjects dosed with Metoclopramide Hydrochloride Orally Disintegrating Tablets: 68 under fasted conditions and 28 under fed conditions.

^4 Number of subjects dosed with metoclopramide tablets: 28 under fed conditions and 44 under fasted conditions.

The most frequently reported adverse reactions (greater than 2%) associated with Metoclopramide Hydrochloride Orally Disintegrating Tablets were: nausea, vomiting, fatigue, somnolence and headache. The most frequently reported adverse reactions (greater than 2%) associated with metoclopramide tablets were: nausea, headache, fatigue, somnolence, and dizziness. The combined data from the fasted BE study and the food-effect study did not demonstrate any significant differences in the adverse event profile for Metoclopramide Hydrochloride Orally Disintegrating Tablets compared to metoclopramide tablets.

6.2 Post-Marketing Experience

The following adverse reactions are from the cumulative post-marketing experience with metoclopramide tablets. Since the reactions are reported voluntarily from a population of uncertain size, it is not always possible to reliably estimate their frequency or establish a causal relationship to drug exposure.

CNS Effects: Restlessness, drowsiness, fatigue, and lassitude occur in approximately 10% of patients receiving the most commonly prescribed dosage of 10 mg four times a day. Insomnia, headache, confusion, dizziness, or depression with suicidal ideation occurs less frequently. The incidence of drowsiness is greater at higher doses. There are isolated reports of seizures without clear-cut relationship to metoclopramide. Rarely, hallucinations have been reported.

Extrapyramidal Syndromes (EPS):

Acute dystonic reactions, the most common type of EPS associated with metoclopramide, occur in approximately 0.2% of patients (1 in 500) treated with 30 to 40 mg of metoclopramide per day. Symptoms include involuntary movements of limbs, facial grimacing, torticollis, oculogyric crisis, rhythmic protrusion of tongue, bulbar type of speech, trismus, opisthotonus (tetanus-like reactions), and rarely, stridor and dyspnea possibly due to laryngospasm; ordinarily these symptoms are readily reversed by diphenhydramine [see Warnings and Precautions (5.1)].

Drug-induced Parkinsonian-like symptoms may include bradykinesia, tremor, cogwheel rigidity, mask-like facies [see Warnings and Precautions (5.2)].

Tardive dyskinesia is most frequently characterized by involuntary movements of the tongue, face, mouth, or jaw, and sometimes by involuntary movements of the trunk and/or extremities; movements may be choreoathetotic in appearance. Motor restlessness (akathisia) may include inability to sit still, pacing, and foot tapping. These symptoms may disappear spontaneously or respond to a reduction in dosage.

Neuroleptic Malignant Syndrome: Rare occurrences of Neuroleptic Malignant Syndrome (NMS) have been reported [see Warnings and Precautions (5.3)].

Endocrine Disturbances: Galactorrhea, amenorrhea, gynecomastia, and impotence secondary to hyperprolactinemia. Fluid retention secondary to transient elevation of aldosterone.

Cardiovascular: Hypotension, hypertension, supraventricular tachycardia, bradycardia, fluid retention, acute congestive heart failure, possible AV block.

Gastrointestinal: Nausea, bowel disturbances, primarily diarrhea.

Hepatic: Rarely, cases of hepatotoxicity characterized by such findings as jaundice and altered liver function tests, when metoclopramide was administered with other drugs with known hepatotoxic potential.

Renal: Urinary frequency and incontinence.

Hematologic: A few cases of neutropenia, leukopenia, or agranulocytosis, generally without clear-cut relationship to metoclopramide. Methemoglobinemia in adults and especially with overdosage in neonates. Sulfhemoglobinemia in adults.

Allergic Reactions: A few cases of rash, urticaria, or bronchospasm, especially in patients with a history of asthma. Rarely, angioneurotic edema, including glossal or laryngeal edema.

Miscellaneous: Visual disturbances. Porphyria.

7 DRUG INTERACTIONS

The effects of metoclopramide on gastrointestinal motility can impact the absorption of other drugs. The known drug-drug interactions are listed below.

7.1 Anticholinergic and Narcotic Analgesic Drugs

The effects of metoclopramide on gastrointestinal motility are antagonized by anticholinergic drugs and narcotic analgesics. Additive sedative effects can occur when metoclopramide is given with alcohol, sedatives, hypnotics, narcotics, or tranquilizers.

7.2 Monoamine Oxidase Inhibitors

Metoclopramide has been shown to release catecholamines in patients with essential hypertension suggesting that it should be used cautiously, if at all, in patients taking monoamine oxidase (MAO) inhibitors.

7.3 Drug Absorption

Absorption of drugs from the stomach may be diminished by metoclopramide (e.g., digoxin), whereas the rate and/or extent of absorption of drugs from the small bowel may be increased (e.g., acetaminophen, tetracycline, levodopa, ethanol, cyclosporine).

7.4 Insulin

Because the action of metoclopramide will hasten the movement of food to the intestines and therefore the rate of absorption, insulin dosage or timing of dosage may require adjustment. Increasing movement of food to the intestines may lead to absorption of less glucose from a meal, hence less glucose in the circulation for a particular dose of administered insulin to act upon, resulting in hypoglycemia.

7.5 Antidepressants, Antipsychotics, and Neuroleptics

Concomitant use of metoclopramide should be avoided in patients taking antidepressants, antipsychotics, and/or neuroleptics that have been associated with extrapyramidal reactions such as tardive dyskinesia or Neuroleptic Malignant Syndrome (NMS) that have occurred in association with metoclopramide [see Warnings and Precautions (5.2), (5.3) and Adverse Reactions (6.2)].

8 USE IN SPECIFIC POPULATIONS

8.1 Pregnancy

Teratogenic Effects: Pregnancy Category B

Reproduction studies have been performed in rats at oral doses about 6 times the maximum recommended human dose calculated on the basis of surface area, and in rabbits at oral doses about 12 times the maximum recommended human dose calculated on the basis of surface area, and have revealed no evidence of impaired fertility or harm to the fetus due to metoclopramide. There are, however, no adequate and well-controlled studies in pregnant women. Because animal reproduction studies are not always predictive of human response, this drug should be used during pregnancy only if clearly needed.

8.2 Labor and Delivery

The use of metoclopramide in labor and delivery has not been studied.

8.3 Nursing Mothers

Metoclopramide is excreted in human milk. Caution should be exercised when metoclopramide is administered to a nursing mother. Because of the potential for serious adverse reactions from metoclopramide in nursing infants and because of the potential for tumorigenicity (including tumor promoting potential in rats), a decision should be made whether to discontinue nursing or to discontinue the drug, taking into account the importance of the drug to the mother.

8.4 Pediatric Use

The safety and effectiveness of Metoclopramide Hydrochloride Orally Disintegrating Tablets in pediatric patients have not been established.

The safety profile of Metoclopramide Hydrochloride Orally Disintegrating Tablets in adults cannot be extrapolated to pediatric patients. Dystonias and other extrapyramidal reactions associated with metoclopramide are more common in the pediatric population than in adults. In addition, neonates have reduced levels of NADH-cytochrome b5 reductase making them more susceptible to methemoglobinemia, a possible side effect of metoclopramide use in neonates.

Pediatric PK

The pharmacodynamics of metoclopramide following oral and intravenous administration in pediatric populations are highly variable and a concentration-effect relationship has not been established. Thus, there are insufficient data to conclude whether the pharmacokinetics of Metoclopramide Hydrochloride Orally Disintegrating Tablets in adults and the pediatric population are similar. Although there are insufficient data to support the efficacy of metoclopramide in pediatric patients with symptomatic gastroesophageal reflux disease (GERD) or cancer chemotherapy-related nausea and vomiting, the pharmacokinetics of metoclopramide have been studied in these patient populations and are summarized as follows.

In an open-label study, six pediatric patients (ranging in age from 3.5 weeks to 5.4 months) with GERD received metoclopramide 0.15 mg/kg oral solution every 6 hours for 10 doses. The mean peak plasma concentration of metoclopramide after the tenth dose was twice the level (56.8 mcg/L) compared to after the first dose (29 mcg/L) indicating drug accumulation with repeated dosing. However, the PK parameters after the tenth dose were comparable to those observed after the first dose for the mean time to reach peak concentrations (2.2 hr); half-life (4.1 hr); clearance (0.67 L/h/kg); and volume of distribution (4.4 L/kg). The youngest patient (3.5 weeks) showed a significantly longer half-life after the first dose (23.1 hr) compared to after the tenth dose (10.3 hr), suggesting the reduced clearance observed at birth may be a reflection of the immature hepatic and renal systems.

8.5 Geriatric Use

Clinical studies of metoclopramide did not include sufficient numbers of subjects aged 65 and over to determine whether elderly subjects respond differently from younger subjects.

The risk of developing drug-induced Parkinsonism due to metoclopramide is dose-related. Geriatric patients should receive the lowest dose that is effective. If drug-induced Parkinsonism symptoms develop in a geriatric patient, Metoclopramide Hydrochloride Orally Disintegrating Tablets should be discontinued. The elderly may be at greater risk for tardive dyskinesia [see Warnings and Precautions (5.1)].

Sedation is a potential adverse event associated with metoclopramide use in the elderly.

Metoclopramide is known to be substantially excreted by the kidney, and the risk of toxic reactions to this drug may be greater in patients with impaired renal function. For these reasons, dose selection for an elderly patient should be cautious, starting at the low end of the dosing range, due to the greater frequency of decreased renal function, concomitant disease, or other drug therapy in the elderly. [see Warnings and Precautions (5.4)].

8.6 Other Special Populations

Patients with NADH-cytochrome b5 reductase deficiency are at an increased risk of developing methemoglobinemia and/or sulfhemoglobinemia when metoclopramide is administered. In patients with G6PD deficiency who experience metoclopramide-induced methemoglobinemia, methylene blue treatment is not recommended.

Since metoclopramide is excreted principally through the kidneys, therapy should be initiated at approximately one-half the recommended dose in those patients whose creatinine clearance is below 40 mL/min. Depending upon clinical efficacy and safety considerations, the dosage may be increased or decreased as appropriate. Metoclopramide has been safely used in patients with advanced liver disease whose renal function was normal.

10 OVERDOSAGE

Symptoms of overdosage may include drowsiness, disorientation, and extrapyramidal reactions. Anticholinergic or anti-Parkinson drugs or antihistamines with anti-cholinergic properties may be helpful in controlling the extrapyramidal reactions. Symptoms are self-limiting and may disappear within 24 hours.

Hemodialysis removes relatively little metoclopramide, probably because of the small amount of the drug in blood relative to tissues. Similarly, continuous ambulatory peritoneal dialysis does not remove significant amounts of drug. It is unlikely that dosage would need to be adjusted to compensate for losses through dialysis. Dialysis is not likely to be an effective method of drug removal in overdose situations.

Unintentional overdose has been reported in infants and children with the use of metoclopramide oral solution. While there was no consistent pattern to the reports associated with these overdoses, events included seizures, extrapyramidal reactions, and lethargy.

Methemoglobinemia has occurred in premature and full-term neonates who were given overdoses of metoclopramide (1 to 4 mg/kg/day orally, intramuscularly or intravenously for 1 to 3 or more days). Methemoglobinemia can be reversed by the intravenous administration of methylene blue. However, methylene blue may cause hemolytic anemia in patients with G6PD deficiency, which may be fatal.

11 DESCRIPTION

Metoclopramide Hydrochloride Orally Disintegrating Tablet is an orally disintegrating tablet formulation of metoclopramide hydrochloride. The 5 mg strength tablets are round, white to off-white, flat faced beveled edge tablet debossed with 'N' on one side and "581" on the other side; it is comprised of 5 mg metoclopramide (as 5.91 mg of metoclopramide hydrochloride). The 10 mg tablets are round, white to off-white, flat faced beveled edge tablet debossed with 'N' on one side and "580" on the other side; it is comprised of 10 mg metoclopramide (as 11.82 mg of metoclopramide hydrochloride).

The active ingredient, metoclopramide hydrochloride, is a white crystalline, odorless substance, freely soluble in water. Chemically, it is 4 amino-5-chloro-N-[2-(diethylamino)ethyl]-2-methoxy benzamide monohydrochloride monohydrate. Its molecular formula is C14H22ClN3O2•HCl•H2O. Its molecular weight is 354.3. The structural formula is shown in Figure 1.

Figure 1

Metoclopramide Hydrochloride Orally Disintegrating Tablets includes the following inactive ingredients: phosphoric acid, mannitol and starch, microcrystalline cellulose, colloidal silicon dioxide, amino methacrylate copolymer, butylated hydroxyanisole, butylated hydroxytoluene, crospovidone, aspartame, N-C mint flavor, magnesium stearate.

12 CLINICAL PHARMACOLOGY

12.1 Mechanism of Action

Metoclopramide stimulates motility of the upper gastrointestinal tract without stimulating gastric, biliary, or pancreatic secretions. While its mode of action is unclear, it appears to sensitize tissues to the action of acetylcholine. The effect on motility is not dependent on intact vagal innervation, but can be abolished by anticholinergic drugs. Metoclopramide increases the tone and amplitude of gastric (especially antral) contractions, relaxes the pyloric sphincter and the duodenal bulb, and increases peristalsis of the duodenum and jejunum resulting in accelerated gastric emptying and intestinal transit. It increases the resting tone of the lower esophageal sphincter. It has little, if any, effect on the motility of the colon or gallbladder.

The antiemetic properties of metoclopramide appear to be a result of its antagonism of central and peripheral dopamine receptors. Dopamine produces nausea and vomiting by stimulation of the medullary chemoreceptor trigger zone (CTZ), and metoclopramide blocks stimulation of the CTZ by agents like l-dopa or apomorphine, which are known to increase dopamine levels or to possess dopamine-like effects. Metoclopramide also abolishes the slowing of gastric emptying caused by apomorphine. Like the phenothiazines and related drugs, which are also dopamine antagonists, metoclopramide produces sedation and may produce extrapyramidal reactions [see Warnings and Precautions (5.2), (5.3)]. Metoclopramide inhibits the central and peripheral effects of apomorphine, induces release of prolactin, and causes a transient increase in circulating aldosterone levels, which may be associated with transient fluid retention.

12.2 Pharmacodynamics

The onset of pharmacological action of metoclopramide is 30 to 60 minutes following an oral dose; pharmacological effects persist for 1 to 2 hours. In patients with gastroesophageal reflux and low LESP (lower esophageal sphincter pressure), single oral doses of metoclopramide produce dose-related increases in LESP. Effects begin at about 5 mg and increase through 20 mg (the largest dose tested). The increase in LESP from a 5 mg dose lasts about 45 minutes and that of a 20 mg dose lasts between 2 and 3 hours. Increased rate of stomach emptying has been observed with single oral doses of 10 mg.

The principal effect of metoclopramide is on symptoms of post-prandial and daytime heartburn with less observed effect on nocturnal symptoms. If symptoms are confined to particular situations, such as following the evening meal, use of metoclopramide as single doses prior to the provocative situation should be considered, rather than using the drug throughout the day. Healing of esophageal ulcers and erosions has been endoscopically demonstrated at the end of a 12-week trial using doses of 15 mg taken four times a day.

As there is no documented correlation between symptoms and healing of esophageal lesions, patients with documented lesions should be monitored endoscopically. For gastroparesis, the usual manifestations of delayed gastric emptying (e.g., nausea, vomiting, heartburn, persistent fullness after meals, and anorexia) appear to respond within different time intervals.

12.3 Pharmacokinetics

Adult PK of Metoclopramide Hydrochloride Orally Disintegrating Tablets

In a randomized, two-arm, two-way crossover study in 44 healthy adult (male and female) fasted subjects, Metoclopramide Hydrochloride Orally Disintegrating Tablet was bioequivalent to Reglan Tablets.

In a food-effect study with 28 subjects, Metoclopramide Hydrochloride Orally Disintegrating Tablets taken immediately after a high-fat meal had a 17% lower peak blood level than when taken after an overnight fast. The time to peak blood levels increased from about 1.75 hours under fasted conditions to 3 hours when taken immediately after a high-fat meal. The extent of metoclopramide absorbed (area under the curve) was comparable whether Metoclopramide Hydrochloride Orally Disintegrating Tablets was administered with or without food. The clinical effect of the decrease in peak plasma level if Metoclopramide Hydrochloride Orally Disintegrating Tablet is inadvertently taken with food is unknown.

Adult PK of Metoclopramide

Metoclopramide is rapidly and well absorbed. Relative to an intravenous dose of 20 mg, the absolute oral bioavailability of metoclopramide is 80% ± 15.5% as demonstrated in a crossover study of 18 subjects. Peak plasma concentrations occur at about 1 to 2 hr after a single oral dose. Similar time to peak is observed after individual doses at steady state. A single dose study of 12 subjects showed that the area under the drug concentration-time curve increases linearly with doses from 20 to 100 mg (results summarized in Table 2). Peak concentrations increase linearly with dose; time to peak concentrations remains the same; whole body clearance is unchanged; and the elimination rate remains the same. The average elimination half-life in individuals with normal renal function is 5 to 6 hr. Linear kinetic processes adequately describe the absorption and elimination of metoclopramide.

Table 2: Adult Pharmacokinetic Data

Parameter | Value
Vd (L/kg) | ~ 3.5
Plasma Protein Binding | ~ 30%
T ½ | 5 to 6 hours
Oral Bioavailability | 80% ± 15.5%

Approximately 85% of the radioactivity of an orally administered dose appears in the urine within 72 hr. Of the 85% eliminated in the urine, about half is present as free or conjugated metoclopramide.

The drug is not extensively bound to plasma proteins (about 30%). The whole body volume of distribution is high (about 3.5 L/kg) which suggests extensive distribution of drug to the tissues.

The in vivo disintegration time (time reported between placing the tablet on the tongue and it completely disintegrated into fine particles) was approximately one minute (with a range of 10 seconds to 14 minutes). In the two clinical trials (N = 96) with a mean ± SD being 76.8 ± 110.6 seconds and a median of 53.5 seconds.

Renal impairment affects the clearance of metoclopramide. In a study with patients with varying degrees of renal impairment, a reduction in creatinine clearance was correlated with a reduction in plasma clearance, renal clearance, non-renal clearance, and increase in elimination half-life. The kinetics of metoclopramide in the presence of renal impairment remained linear. The reduction in clearance as a result of renal impairment suggests that reduction of maintenance dosage should be done to avoid drug accumulation.

13 NONCLINICAL TOXICOLOGY

13.1 Carcinogenesis, Mutagenesis, Impairment of Fertility

A 77-week study was conducted in rats with oral doses up to 40 mg/kg/day (about 5 times the maximum recommended human dose on surface area basis). Metoclopramide elevates prolactin levels and the elevation persists during chronic administration. Tissue culture experiments indicate that approximately one-third of human breast cancers are prolactin-dependent in vitro, a factor of potential importance if the prescription of metoclopramide is contemplated in a patient with previously detected breast cancer. Although disturbances such as galactorrhea, amenorrhea, gynecomastia, and impotence have been reported with prolactin-elevating drugs, the clinical significance of elevated serum prolactin levels is unknown for most patients. An increase in mammary neoplasms has been found in rodents after chronic administration of prolactin-stimulating neuroleptic drugs and metoclopramide. Neither clinical studies nor epidemiologic studies conducted to date, however, have shown an association between chronic administration of these drugs and mammary tumorigenesis; the available evidence is too limited to be conclusive at this time.

In a rat model for assessing the tumor promotion potential, a two-week oral treatment with metoclopramide at a dose of 260 mg/kg/day (about 35 times the maximum recommended human dose based on body surface area) enhanced the tumorigenic effect of N-nitrosodiethylamine.

Metoclopramide was positive in the in vitro Chinese hamster lung cell / HGPRT forward mutation assay for mutagenic effects and the in vitro human lymphocyte chromosome aberration assay for clastogenic effects. It was negative in the in vitro Ames mutation assay, the in vitro unscheduled DNA synthesis (UDS) assay with rat and human hepatocytes and the in vivo rat micronucleus assay.

Metoclopramide at intramuscular doses up to 20 mg/kg/day (about 3 times the maximum recommended human dose based on body surface area) was found to have no effect on fertility and reproductive performance of male and female rats.

16 HOW SUPPLIED/STORAGE AND HANDLING

Metoclopramide Hydrochloride Orally Disintegrating Tablets 5 mg strength are round, white to off-white, flat faced beveled edge tablet debossed with 'N' on one side and "581" on the other side; it is comprised of 5 mg metoclopramide (as 5.91 mg of metoclopramide hydrochloride). These are packaged in blister cards as follows:

Box of 10 (1x10) NDC 40032-581-31

Metoclopramide Hydrochloride Orally Disintegrating Tablets 10 mg are round, white to off-white, flat faced beveled edge tablet debossed with 'N' on one side and "580" on the other side; it is comprised of 10 mg metoclopramide (as 11.82 mg of metoclopramide hydrochloride). These are packaged in blister cards as follows:

Box of 10 (1x10) NDC 40032-580-31

Tablets should be stored at controlled room temperature, between 20°C and 25°C (68°F and 77°F).

17 PATIENT COUNSELING INFORMATION

- Instruct patients to take Metoclopramide Hydrochloride Orally Disintegrating Tablets at least 30 minutes before eating and at bedtime.
- A patient Medication Guide is available for Metoclopramide Hydrochloride Orally Disintegrating Tablets and printed at the end of the prescribing information. Instruct patients, families, and caregivers to read the Medication Guide and assist them in understanding its contents.
- Inform patients or their caregivers of serious potential issues associated with metoclopramide use such as tardive dyskinesia, extrapyramidal symptoms, and neuroleptic malignant syndrome. Advise patients to inform their physician if symptoms associated with these disorders occur during or after treatment with Metoclopramide Hydrochloride Orally Disintegrating Tablets.
- Inform patients that Metoclopramide Hydrochloride Orally Disintegrating Tablets may cause drowsiness, dizziness, or otherwise impair mental alertness or physical abilities required for the performance of hazardous tasks such as operating machinery or driving a motor vehicle. Sedation may be more pronounced in the elderly.
- Inform patients that the most common adverse reactions in patients treated with Metoclopramide Hydrochloride Orally Disintegrating Tablets or other metoclopramide-containing products are headache, nausea, vomiting, tiredness, sleepiness, dizziness, and restlessness.

Manufactured by:

Novel Laboratories, Inc

Somerset, NJ 08873

USA

PI5800000102

Rev. 05/2017

SPL MEDGUIDE

Medication Guide

Metoclopramide Hydrochloride Orally Disintegrating Tablets

Phenylketonurics:

Phenylalanine is a component of aspartame. Each 5 mg and 10 mg Metoclopramide Hydrochloride Orally Disintegrating Tablets contains 4.7 mg of phenylalanine.

Read the Medication Guide that comes with Metoclopramide Hydrochloride Orally Disintegrating Tablets before you take it and each time you get a refill. There may be new information. If you take another product that contains metoclopramide (such as REGLAN tablets, REGLAN ODT, REGLAN injection or metoclopramide oral solution), you should read the Medication Guide that comes with that product. Some of the information may be different. This Medication Guide does not take the place of talking with your doctor about your medical condition or your treatment.

What is the most important information I should know about Metoclopramide Hydrochloride Orally Disintegrating Tablets?

Metoclopramide Hydrochloride Orally Disintegrating Tablets can cause serious side effects, including:

Tardive Dyskinesia (abnormal muscle movements) These movements happen mostly in the face muscles. You cannot control these movements. They may not go away even after stopping Metoclopramide Hydrochloride Orally Disintegrating Tablets. There is no treatment for tardive dyskinesia, but symptoms may lessen or go away over time after you stop taking Metoclopramide Hydrochloride Orally Disintegrating Tablets.

Your chances for getting tardive dyskinesia go up:

- the longer you take Metoclopramide Hydrochloride Orally Disintegrating Tablets and the more Metoclopramide Hydrochloride Orally Disintegrating Tablets you take. You should not take Metoclopramide Hydrochloride Orally Disintegrating Tablets for more than 12 weeks.
- if you are older, especially if you are an older woman
- if you have diabetes

It is not possible for your doctor to know if you will get tardive dyskinesia if you take Metoclopramide Hydrochloride Orally Disintegrating Tablets.

Call your doctor right away if you have movements you can not stop or control, such as:

- lip smacking, chewing, or puckering of your lips
- frowning or scowling
- sticking out your tongue
- blinking and moving your eyes
- shaking of your arms and legs

See the section "What are the possible side effects of Metoclopramide Hydrochloride Orally Disintegrating Tablets?" for more information about side effects.

What is Metoclopramide Hydrochloride Orally Disintegrating Tablets?

Metoclopramide Hydrochloride Orally Disintegrating Tablets is a prescription medicine used in adults:

- for 4 to 12 weeks to relieve heartburn symptoms of gastroesophageal reflux disease (GERD) when certain other treatments do not work.
- to relieve the symptoms of slow stomach emptying in people with diabetes.

It is not known if Metoclopramide Hydrochloride Orally Disintegrating Tablets is safe or works in children.

Who should not take Metoclopramide Hydrochloride Orally Disintegrating Tablets?

Do not take Metoclopramide Hydrochloride Orally Disintegrating Tablets if you:

- have stomach or intestine problems that could get worse with Metoclopramide Hydrochloride Orally Disintegrating Tablets, such as bleeding, blockage or a tear in your stomach or bowel wall
- have an adrenal tumor called pheochromocytoma
- are allergic to metoclopramide or any of the ingredients in Metoclopramide Hydrochloride Orally Disintegrating Tablets. See the end of this Medication Guide for a list of ingredients in Metoclopramide Hydrochloride Orally Disintegrating Tablets.
- take medicines that can cause uncontrolled movements, such as medicines for mental illness.
- have seizures

What should I tell my doctor before taking Metoclopramide Hydrochloride Orally Disintegrating Tablets?

Before you take Metoclopramide Hydrochloride Orally Disintegrating Tablets, tell your doctor if you:

- have kidney or liver disease
- have depression or mental illness
- have high blood pressure
- have heart failure or heart rhythm problems
- have diabetes. Your dose of insulin may need to be changed.
- have Parkinson's disease
- have any other medical conditions
- drink alcohol
- are pregnant or plan to become pregnant. It is not known if Metoclopramide Hydrochloride Orally Disintegrating Tablets will harm your unborn baby.
- are breast-feeding or plan to breast-feed. Metoclopramide Hydrochloride Orally Disintegrating Tablets can pass into your milk and may harm your baby. You and your doctor should decide if you will take Metoclopramide Hydrochloride Orally Disintegrating Tablets or breast-feed. You should not do both.

Tell your doctor about all the medicines you take, including prescription and non-prescription medicines, vitamins, and herbal supplements. Metoclopramide Hydrochloride Orally Disintegrating Tablets and some medicines can affect each other and may not work as well, or cause possible side effects. Do not start any new medicine while taking Metoclopramide Hydrochloride Orally Disintegrating Tablets until you talk with your doctor.

Especially tell your doctor if you take:

- another medicine that contains metoclopramide, such as REGLAN tablets, REGLAN ODT, or metoclopramide oral syrup
- a blood pressure medicine
- a medicine for depression, especially a monoamine oxidase inhibitor (MAOI)
- an anti-psychotic medicine
- insulin
- medicines that can make you sleepy, such as anti-anxiety medicines, sleep medicines, and narcotics.

Ask your doctor or pharmacist if you are not sure if your medication is listed above. Know the medicines you take. Keep a list of your medicines to show your doctor and pharmacist when you get new medicine.

How should I take Metoclopramide Hydrochloride Orally Disintegrating Tablets?

- Metoclopramide Hydrochloride Orally Disintegrating Tablets comes as a tablet that melts in your mouth.
- Take Metoclopramide Hydrochloride Orally Disintegrating Tablets exactly as prescribed by your doctor. Do not change your dose unless your doctor tells you to.
- You should not take Metoclopramide Hydrochloride Orally Disintegrating Tablets for more than 12 weeks.
- Take Metoclopramide Hydrochloride Orally Disintegrating Tablets at least 30 minutes before eating and at bedtime.

To take Metoclopramide Hydrochloride Orally Disintegrating Tablets:

1. Leave the tablet in the sealed blister Metoclopramide Hydrochloride Orally Disintegrating Tablets pack until you are ready to take it.
2. Use dry hands to open a blister and take out a tablet. If the tablet breaks or crumbles throw it away and take a new tablet out of the blister pack.
3. Put the tablet on your tongue right away. Let it melt and then swallow. You do not need water to take Metoclopramide Hydrochloride Orally Disintegrating Tablets.

If you take too much Metoclopramide Hydrochloride Orally Disintegrating Tablets, call your doctor or Poison Control Center.

What should I avoid while taking Metoclopramide Hydrochloride Orally Disintegrating Tablets?

- Do not drink alcohol while taking Metoclopramide Hydrochloride Orally Disintegrating Tablets. Alcohol may make some side effects of Metoclopramide Hydrochloride Orally Disintegrating Tablets worse, such as feeling sleepy.
- Do not drive, work with machines, or do dangerous tasks until you know how Metoclopramide Hydrochloride Orally Disintegrating Tablets affects you. Metoclopramide Hydrochloride Orally Disintegrating Tablets may cause sleepiness.

What are the possible side effects of Metoclopramide Hydrochloride Orally Disintegrating Tablets?

Metoclopramide Hydrochloride Orally Disintegrating Tablets can cause serious side effects, including:

- Tardivedyskinesia (abnormal muscle movements) See "What is the most important information I should know about Metoclopramide Hydrochloride Orally Disintegrating Tablets?"
- Uncontrolled spasms of your face and neck muscles, or muscles of your body, arms, and legs (dystonia). These muscle spasms can cause abnormal movements and body positions. These spasms usually start within the first 2 days of treatment. These spasms happen more often in children and adults younger than 30.
- Depression, thoughts about suicide, and suicide. Some people who take Metoclopramide Hydrochloride Orally Disintegrating Tablets may become depressed. You may have thoughts about hurting or killing yourself. Some people who have taken metoclopramide products have ended their own lives (suicide).
- Neuroleptic Malignant Syndrome (NMS). NMS is a rare but very serious condition that can happen with Metoclopramide Hydrochloride Orally Disintegrating Tablets. NMS can cause death and must be treated in a hospital. Symptoms of NMS include: high fever, stiff muscles, problems thinking, very fast or uneven heartbeat, and increased sweating.
- Parkinsonism. Symptoms include slight shaking, body stiffness, trouble moving or keeping your balance. If you have Parkinson's Disease, your symptoms may become worse while you are taking Metoclopramide Hydrochloride Orally Disintegrating Tablets.
- High blood pressure. Metoclopramide Hydrochloride Orally Disintegrating Tablets can cause your blood pressure to increase.
- Too much body water. People who have certain liver problems or heart failure and take Metoclopramide Hydrochloride Orally Disintegrating Tablets may hold too much water in their body (fluid retention). Tell your doctor right away if you have sudden weight gain, or swelling of your hands, legs, or feet.

Call your doctor and get medical help right away if you:

- feel depressed or have thoughts about hurting or killing yourself
- have high fever, stiff muscles, problems thinking, very fast or uneven heartbeat, and increased sweating
- have muscle movements you cannot stop or control
- have muscle movements that are new or unusual

The most common side effects of Metoclopramide Hydrochloride Orally Disintegrating Tablets are:

- headache
- nausea
- vomiting
- tiredness
- sleepiness

You may have more side effects the longer you take Metoclopramide Hydrochloride Orally Disintegrating Tablets and the more Metoclopramide Hydrochloride Orally Disintegrating Tablets you take.

You may still have side effects after you stop Metoclopramide Hydrochloride Orally Disintegrating Tablets. You may have symptoms from stopping (withdrawal) Metoclopramide Hydrochloride Orally Disintegrating Tablets such as headaches, and feeling dizzy or nervous.

Tell your doctor about any side effects that bother you or do not go away. These are not all the possible side effects of Metoclopramide Hydrochloride Orally Disintegrating Tablets.

Call your doctor for medical advice about side effects. You may report side effects to FDA at 1–800–FDA-1088.

How do I store Metoclopramide Hydrochloride Orally Disintegrating Tablets?

- Store Metoclopramide Hydrochloride Orally Disintegrating Tablets at room temperature, between 68°F to 77°F (20°C to 25°C).
- Keep Metoclopramide Hydrochloride Orally Disintegrating Tablets away from moisture.
- Throw away any Metoclopramide Hydrochloride Orally Disintegrating Tablets that is not used.

Keep Metoclopramide Hydrochloride Orally Disintegrating Tablets and all medicines away from children.

General information about Metoclopramide Hydrochloride Orally Disintegrating Tablets

Medicines are sometimes prescribed for purposes other than those listed in a Medication Guide. Do not use Metoclopramide Hydrochloride Orally Disintegrating Tablets for a condition for which it was not prescribed. Do not give Metoclopramide Hydrochloride Orally Disintegrating Tablets to other people, even if they have the same symptoms that you have. It may harm them.

This Medication Guide summarizes the most important information about Metoclopramide Hydrochloride Orally Disintegrating Tablets. If you would like more information about Metoclopramide Hydrochloride Orally Disintegrating Tablets, talk with your doctor. You can ask your doctor or pharmacist for information about Metoclopramide Hydrochloride Orally Disintegrating Tablets that is written for health professionals.

What are the ingredients in Metoclopramide Hydrochloride Orally Disintegrating Tablets?

Active ingredients: metoclopramide hydrochloride

Inactive ingredients: phosphoric acid, mannitol and starch, microcrystalline cellulose, colloidal silicon dioxide, amino methacrylate copolymer, butylated hydroxyanisole, butylated hydroxytoluene, crospovidone, aspartame, N-C mint flavor, magnesium stearate.

Novel Laboratories, Inc

Somerset, NJ 08873

USA

PI5800000102

Rev 05/2017

This Medication Guide has been approved by the U.S. Food and Drug Administration.

PACKAGE LABEL.PRINCIPAL DISPLAY PANEL

NDC 40032-580-30

Blister Pack

Metoclopramide Hydrochloride Orally Disintegrating Tablets

10 mg

NDC 40032-580-31

Carton

Metoclopramide Hydrochloride Orally Disintegrating Tablets

10 mg

Front Panel

Back Panel:

NDC 40032-581-30

Blister Pack

Metoclopramide Hydrochloride Orally Disintegrating Tablets

5 mg

NDC 40032-581-31

Carton

Metoclopramide Hydrochloride Orally Disintegrating Tablets

5 mg

Front Panel

Back Panel